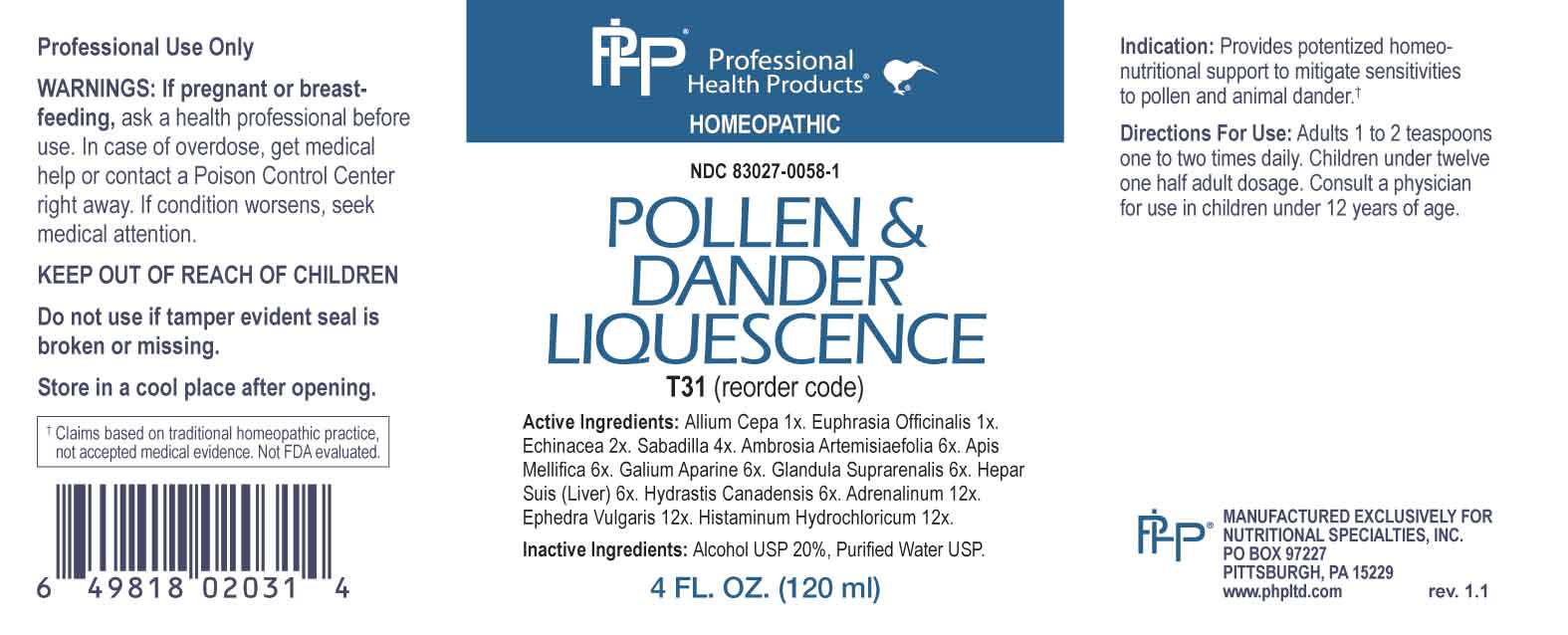 DRUG LABEL: Pollen and Dander Liquescence
NDC: 83027-0058 | Form: LIQUID
Manufacturer: Nutritional Specialties, Inc.
Category: homeopathic | Type: HUMAN OTC DRUG LABEL
Date: 20251006

ACTIVE INGREDIENTS: ONION 1 [hp_X]/1 mL; EUPHRASIA STRICTA 1 [hp_X]/1 mL; ECHINACEA ANGUSTIFOLIA WHOLE 2 [hp_X]/1 mL; SCHOENOCAULON OFFICINALE SEED 4 [hp_X]/1 mL; AMBROSIA ARTEMISIIFOLIA WHOLE 6 [hp_X]/1 mL; APIS MELLIFERA 6 [hp_X]/1 mL; GALIUM APARINE WHOLE 6 [hp_X]/1 mL; BOS TAURUS ADRENAL GLAND 6 [hp_X]/1 mL; PORK LIVER 6 [hp_X]/1 mL; GOLDENSEAL 6 [hp_X]/1 mL; EPINEPHRINE 12 [hp_X]/1 mL; EPHEDRA DISTACHYA FLOWERING TWIG 12 [hp_X]/1 mL; HISTAMINE DIHYDROCHLORIDE 12 [hp_X]/1 mL
INACTIVE INGREDIENTS: WATER; ALCOHOL

DRUG FACTS:

ACTIVE INGREDIENTS:

Allium Cepa 1X, Euphrasia Officinalis 1X, Echinacea 2X, Sabadilla 4X, Ambrosia Artemisiaefolia 6X, Apis Mellifica 6X, Galium Aparine 6X, Glandula Suprarenalis 6X, Hepar Suis (Liver) 6X, Hydrastis Canadensis 6X, Adrenalinum 12X, Ephedra Vulgaris 12X, Histaminum Hydrochloricum 12X.

PURPOSE:

Provides potentized homeo-nutritional support to mitigate sensitivities to pollen and animal dander.†

†Claims based on traditional homeopathic practice, not accepted medical evidence. Not FDA evaluated.

WARNINGS:

Professional Use Only

If pregnant or breast-feeding, ask a health professional before use.

In case of overdose, get medical help or contact a Poison Control Center right away.

If condition worsens, seek medical attention.

KEEP OUT OF REACH OF CHILDREN

Do not use if tamper evident seal is broken or missing.

Store in a cool place after opening

KEEP OUT OF REACH OF CHILDREN:

In case of overdose, get medical help or contact a Poison Control Center right away.

DIRECTIONS:

Adults 1 to 2 teaspoons one to two times daily. Children under twelve one half adult dosage. Consult a physician for use in children under 12 years of age.

INDICATIONS:

Provides potentized homeo-nutritional support to mitigate sensitivities to pollen and animal dander.†

†Claims based on traditional homeopathic practice, not accepted medical evidence. Not FDA evaluated.

INACTIVE INGREDIENTS:

Alcohol USP 20%, Purified Water USP.

QUESTIONS:

MANUFACTURED EXCLUSIVELY FOR

NUTRITIONAL SPECIALTIES, INC.

PO BOX 97227

PITTSBURG, PA 15229

www.phpltd.com

PACKAGE LABEL DISPLAY:

Professional

Health Products

HOMEOPATHIC

NDC 83027-0058-1

POLLEN &

DANDER

LIQUESCENCE

4 FL. OZ (120 ml)